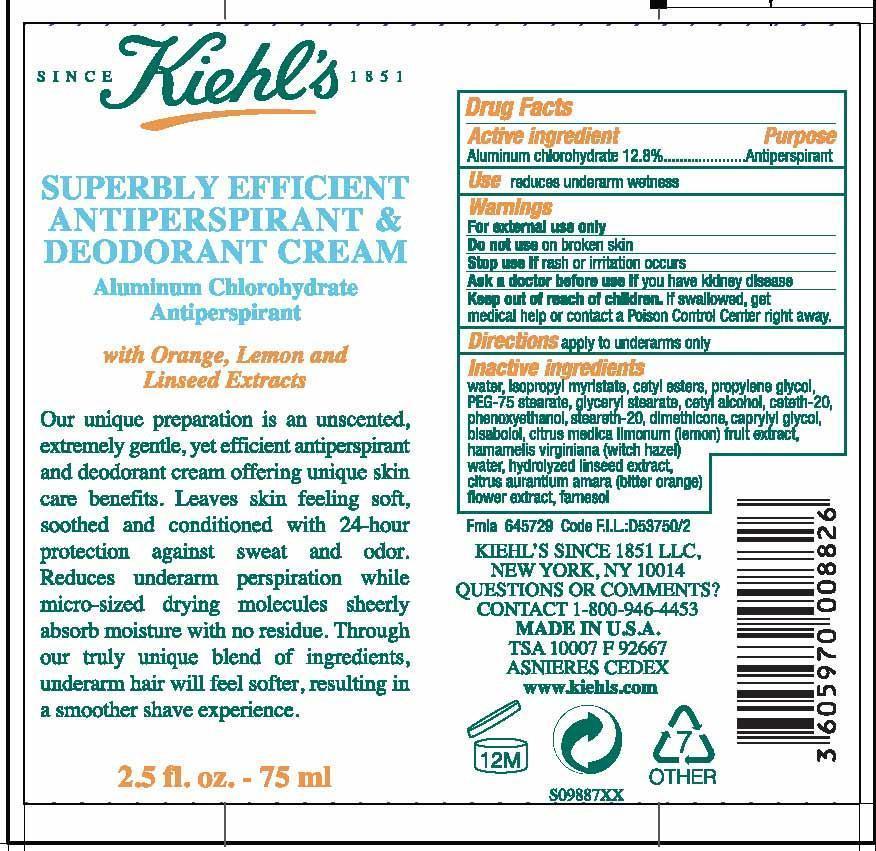 DRUG LABEL: Kiehls Since 1851 Superbly Efficient Antiperspirant and Deodorant
NDC: 49967-882 | Form: CREAM
Manufacturer: L'Oreal USA Products Inc
Category: otc | Type: HUMAN OTC DRUG LABEL
Date: 20231230

ACTIVE INGREDIENTS: ALUMINUM CHLOROHYDRATE 128 mg/1 mL
INACTIVE INGREDIENTS: WATER; ISOPROPYL MYRISTATE; CETYL ESTERS WAX; PROPYLENE GLYCOL; PEG-75 STEARATE; GLYCERYL MONOSTEARATE; CETYL ALCOHOL; CETETH-20; PHENOXYETHANOL; STEARETH-20; DIMETHICONE; CAPRYLYL GLYCOL; LEVOMENOL; LEMON; HAMAMELIS VIRGINIANA TOP WATER; CITRUS AURANTIUM FLOWER; FARNESOL

Active ingredient

Aluminum chlorohydrate 12.8%

Purpose

Antiperspirant

Use

reduces underarm wetness

Warnings

For external use only

Do not use

on broken skin

Stop use if

rash or irritation occurs

Ask a doctor before use if

you have kidney disease

Keep out of reach of children.

If swallowed, get medical help or contact a Poison Control Center right away.

Directions

apply to underarms only

Inactive ingredients

water, isopropyl myristate, cetyl esters, propylene glycol, PEG-75 stearate, glyceryl stearate, cetyl alcohol, ceteth-20, phenoxyethanol, steareth-20, dimethicone, caprylyl glycol, bisabolol, citrus medica limonum (lemon) fruit extract, hamamelis virginiana (witch hazel) water, hydrolyzed linseed extract, citrus aurantium amara (bitter orange) flower extract, farnesol